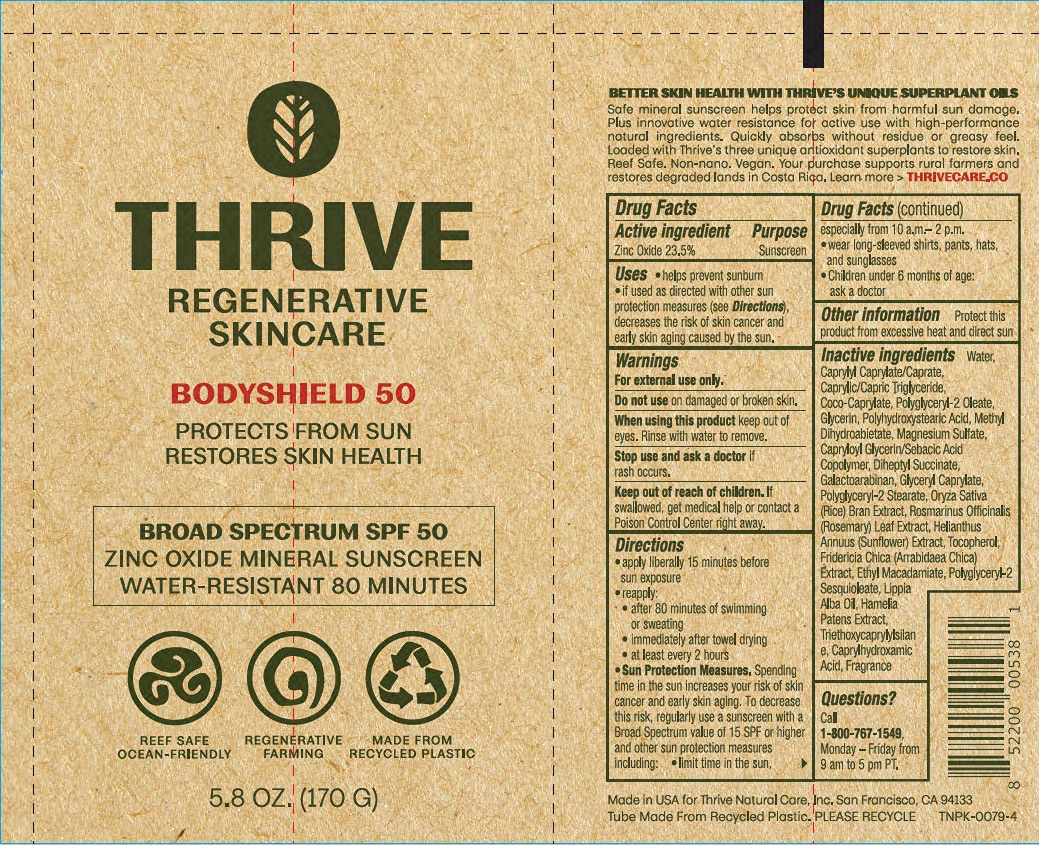 DRUG LABEL: Thrive Bodyshield 50 SPF 50
NDC: 84138-0003 | Form: CREAM
Manufacturer: Thrive Natural Care, Inc
Category: otc | Type: HUMAN OTC DRUG LABEL
Date: 20251023

ACTIVE INGREDIENTS: ZINC OXIDE 23.5 g/100 g
INACTIVE INGREDIENTS: RICE BRAN; TOCOPHEROL; MEDIUM-CHAIN TRIGLYCERIDES; POLYGLYCERYL-2 OLEATE; CAPRYLYL CAPRYLATE/CAPRATE; METHYL DIHYDROABIETATE; CAPRYLOYL GLYCERIN/SEBACIC ACID COPOLYMER (2000 MPA.S); POLYHYDROXYSTEARIC ACID (2300 MW); GALACTOARABINAN; COCO-CAPRYLATE; CAPRYLHYDROXAMIC ACID; LIPPIA ALBA TOP OIL; HAMELIA PATENS LEAF; ETHYL MACADAMIATE; TRIETHOXYCAPRYLYLSILANE; GLYCERIN; ROSEMARY; SUNFLOWER OIL; FRIDERICIA CHICA LEAF; WATER; GLYCERYL CAPRYLATE; DIHEPTYL SUCCINATE; POLYGLYCERYL-2 STEARATE; POLYGLYCERYL-2 SESQUIOLEATE; MAGNESIUM SULFATE, UNSPECIFIED FORM

Thrive Bodyshield 50 SPF 50

Active Ingredient

Zinc Oxide 23.5%

Purpose

Sunscreen

Uses

helps prevent sunburn

if used as directed with other sun protection measures (see Directions), decreases the risk of skin cancer and early skin aging caused by the sun.

Warnings

For external use only.

Do not use

on damaged or broken skin.

When using this product

keep out of eyes. Rinse with water to remove.

Stop use and ask a doctor if

rash occurs.

Keep out of reach of children.

If swallowed, get medical help or contact a Poison Control Center right away.

Directions

apply liberally 15 minutes before sun exposure

use a water resistant sunscreen if swimming or sweating

reapply

- after 80 minutes of swimming or sweating
- immediately after towel drying
- at least every 2 hours

Sun Protection Measures. Spending time in the sun increases your risk of skin cancer and early skin aging. To decrease this risk, regularly use a sunscreen with a Broad Spectrum value of 15 SPF or higher and other sun protection measures including:

- limit time in the sun, especially from 10 a.m.- 2 p.m.
- wear long-sleeved shirts, pants, hats and sunglasses

Children under 6 months of age: ask a doctor

Other information

Protect this product from excessive heat and direct sun

Inactive ingredients

Water, Caprylyl Caprylate/Caprate, Caprylic/Capric Triglyceride, Coco-Caprylate, Polyglyceryl-2 Oleate, Glycerin, Polyhydroxystearic Acid, Methyl Dihydroabietate, Magnesium Sulfate, Capryloyl Glycerin/Sebacic Acid Copolymer, Diheptyl Succinate, Galactoarabinan, Glyceryl Caprylate, Polyglyceryl-2 Stearate, Oryza Sativa (Rice) Bran Extract, Rosmarinus Officinalis (Rosemary) Leaf Extract, Helianthus Annuus (Sunflower) Extract, Tocopherol, Fridericia Chica (Arrabidaea Chica) Extract, Ethyl Macadamiate, Polyglyceryl-2 Sesquioleate, Lippia Alba Oil, Hamelia Patens Extract, Triethoxycaprylylsilane, Caprylhydroxamic Acid, Fragrance.

Questions?

Call 1-800-767-1549, Monday - Friday from 9 am PT to 5 pm PT

Principal Display Panel

THRIVE

REGENERATIVE

SKINCARE

BODYSHIELD 50

PROTECTS FROM SUN

RESTORES SKIN HEALTH

BROAD SPECTRUM SPF 50

ZINC OXIDE MINERAL SUNSCREEN

WATER-RESISTANT 80 MINUTES

REEF SAFE

OCEAN-FRIENDLY

REGENERATIVE

FARMING

MADE FROM

RECYCLED PLASTIC

5.8 OZ (170 G)